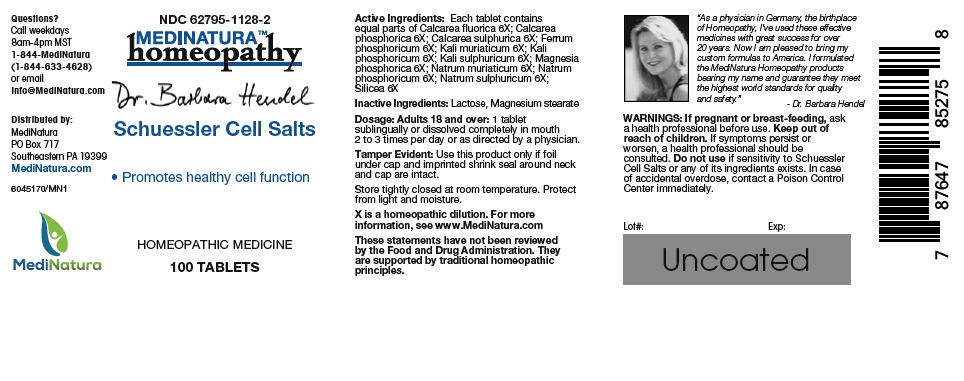 DRUG LABEL: Hendel Schuessler Cell Salts
NDC: 62795-1128 | Form: TABLET
Manufacturer: MediNatura Inc
Category: homeopathic | Type: HUMAN OTC DRUG LABEL
Date: 20220822

ACTIVE INGREDIENTS: CALCIUM FLUORIDE 6 [hp_X]/1 1; TRIBASIC CALCIUM PHOSPHATE 6 [hp_X]/1 1; CALCIUM SULFATE ANHYDROUS 6 [hp_X]/1 1; FERRUM PHOSPHORICUM 6 [hp_X]/1 1; POTASSIUM CHLORIDE 6 [hp_X]/1 1; DIBASIC POTASSIUM PHOSPHATE 6 [hp_X]/1 1; POTASSIUM SULFATE 6 [hp_X]/1 1; MAGNESIUM PHOSPHATE, DIBASIC 6 [hp_X]/1 1; SODIUM CHLORIDE 6 [hp_X]/1 1; SODIUM PHOSPHATE, DIBASIC 6 [hp_X]/1 1; SODIUM SULFATE 6 [hp_X]/1 1; SILICON DIOXIDE 6 [hp_X]/1 1
INACTIVE INGREDIENTS: LACTOSE MONOHYDRATE; MAGNESIUM STEARATE

Hendel Schuessler Cell Salts

WARNINGS

If pregnant or breast-feeding, ask a health professional before use. Keep out of reach of children. If symptoms persist or worsen, a health professional should be consulted. Do not use if sensitivity to Schuessler Cell Salts or any of its ingredients exists. In case of accidental overdose, contact a Poison Control Center immediately.

KEEP OUT OF REACH OF CHILDREN

INDICATIONS

Promotes Healthy cell Function

INGREDIENTS

Each tablet contains equal parts of Calcarea fluorica 6X, Calcarea phosphorica 6X, Calcarea sulphurica 6X, Ferrum phoshporicum 6X, Kali muriatcum 6X, Kali phosphoricum 6X, Kali sulphuricum 6X, Magnesia phosphorica 6X, Natrum muriaticum 6X, Natrum phosphoricum 6X, Natrum sulphuricum 6X, Silicea 6X.

INACTIVE INGREDIENT

Lactose, Magnesium stearate

DIRECTIONS

Adults 18 and over: 1 tablet sublingually or dissolved completely in mouth 2 to 3 times per day or as directed by a physician

USES

For the temporary relief of:
• Promotes Healthy cell Function

PACKAGE LABEL

Add image transcription here...